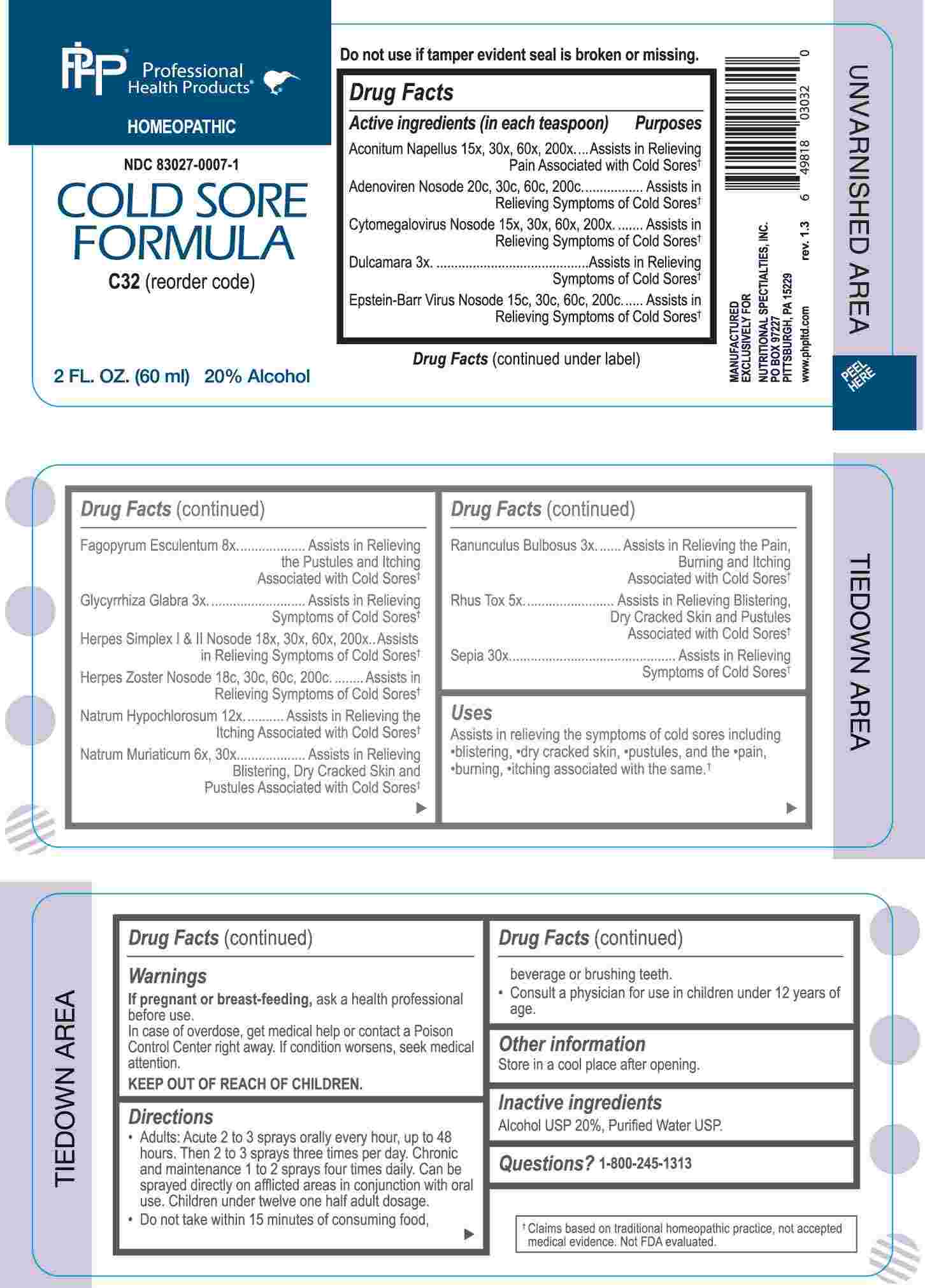 DRUG LABEL: Cold Sore Formula
NDC: 83027-0007 | Form: SPRAY
Manufacturer: Nutritional Specialties, Inc.
Category: homeopathic | Type: HUMAN OTC DRUG LABEL
Date: 20241031

ACTIVE INGREDIENTS: SOLANUM DULCAMARA TOP 3 [hp_X]/1 mL; GLYCYRRHIZA GLABRA 3 [hp_X]/1 mL; RANUNCULUS BULBOSUS WHOLE 3 [hp_X]/1 mL; TOXICODENDRON PUBESCENS LEAF 5 [hp_X]/1 mL; SODIUM CHLORIDE 6 [hp_X]/1 mL; FAGOPYRUM ESCULENTUM WHOLE 8 [hp_X]/1 mL; SODIUM HYPOCHLORITE 12 [hp_X]/1 mL; ACONITUM NAPELLUS WHOLE 15 [hp_X]/1 mL; HUMAN HERPESVIRUS 5 15 [hp_X]/1 mL; HUMAN HERPESVIRUS 1 18 [hp_X]/1 mL; HUMAN HERPESVIRUS 2 18 [hp_X]/1 mL; SEPIA OFFICINALIS JUICE 30 [hp_X]/1 mL; HUMAN HERPESVIRUS 4 15 [hp_C]/1 mL; HUMAN HERPESVIRUS 3 18 [hp_C]/1 mL; HUMAN ADENOVIRUS E SEROTYPE 4 STRAIN CL-68578 ANTIGEN 20 [hp_C]/1 mL
INACTIVE INGREDIENTS: WATER; ALCOHOL

DRUG FACTS:

ACTIVE INGREDIENTS:

(in each teaspoon) Aconitum Napellus 15X, 30X, 60X, 200X, Adenoviren Nosode 20C, 30C, 60C, 200C, Cytomegalovirus Nosode 15X, 30X, 60X, 200X, Dulcamara 3X, Epstein-Barr Virus Nosode 15C, 30C, 60C, 200C, Fagopyrum Esculentum 8X, Glycyrrhiza Glabra 3X, Herpes Simplex I and II Nosode 18X, 30X, 60X, 200X, Herpes Zoster Nosode 18C, 30C, 60C, 200C, Natrum Hypochlorosum 12X, Natrum Muriaticum 6X, 30X, Ranunculus Bulbosus 3X, Rhus Tox 5X, Sepia 30X.

PURPOSE:

Aconitum Napellus – Assists in Relieving Pain Associated with Cold Sores,† Adenoviren Nosode - Assists in Relieving Symptoms of Cold Sores,† Cytomegalovirus Nosode - Assists in Relieving Symptoms of Cold Sores,† Dulcamara - Assists in Relieving Symptoms of Cold Sores,† Epstein-Barr Virus Nosode - Assists in Relieving Symptoms of Cold Sores,† Fagopyrum Esculentum – Assists in Relieving the Pustules and Itching Associated with Cold Sores,† Glycyrrhiza Glabra - Assists in Relieving Symptoms of Cold Sores,† Herpes Simplex I and II Nosode - Assists in Relieving Symptoms of Cold Sores,† Herpes Zoster Nosode - Assists in Relieving Symptoms of Cold Sores,† Natrum Hypochlorosum – Assists in Relieving the Itching Associated with Cold Sores,† Natrum Muriaticum – Assists in Relieving Blistering, Dry Cracked Skin and Pustules Associated with Cold Sores,† Ranunculus Bulbosus – Assists in Relieving the Pain, Burning and Itching Associated with Cold Sores,† Rhus Tox – Assists in Relieving Blistering, Dry Cracked Skin and Pustules Associated with Cold Sores,† Sepia – Assists in Relieving Symptoms of Cold Sores.

†Claims based on traditional homeopathic practice, not accepted medical evidence. Not FDA evaluated.

USES:

Assists in relieving the symptoms of cold sores including

•blistering, •dry cracked skin, •pustules, and the •pain,

•burning, •itching associated with the same.†

†Claims based on traditional homeopathic practice, not accepted medical evidence. Not FDA evaluated.

WARNINGS:

If pregnant or breast-feeding, ask a health professional before use.

In case of overdose, get medical help or contact a Poison Control Center right away.

If condition worsens, seek medical attention.

KEEP OUT OF REACH OF CHILDREN

Do not use if tamper evident seal is broken or missing.

Store in a cool place after opening

KEEP OUT OF REACH OF CHILDREN:

In case of overdose, get medical help or contact a Poison Control Center right away.

DIRECTIONS:

• Adults: Acute 2 to 3 sprays orally every hour, up to 48 hours. Then 2 to 3 sprays three times per day. Chronic and maintenance 1 to 2 sprays four times daily. Can be sprayed directly on afflicted areas in conjunction with oral use. Children under twelve one half adult dosage.

• Do not take within 15 minutes of consuming food, beverage or brushing teeth.

• Consult a physician for use in children under 12 years of age.

INACTIVE INGREDIENTS:

Alcohol USP 20%, Purified Water USP.

QUESTIONS:

MANUFACTURED EXCLUSIVELY FOR

NUTRITIONAL SPECIALTIES, INC.

PO BOX 97227

PITTSBURG, PA 15229

www.phpltd.com

PACKAGE LABEL DISPLAY:

Professional

Health Products

HOMEOPATHIC

NDC 83027-0007-1

COLD SORE

FORMULA

2 FL. OZ (60 ml)